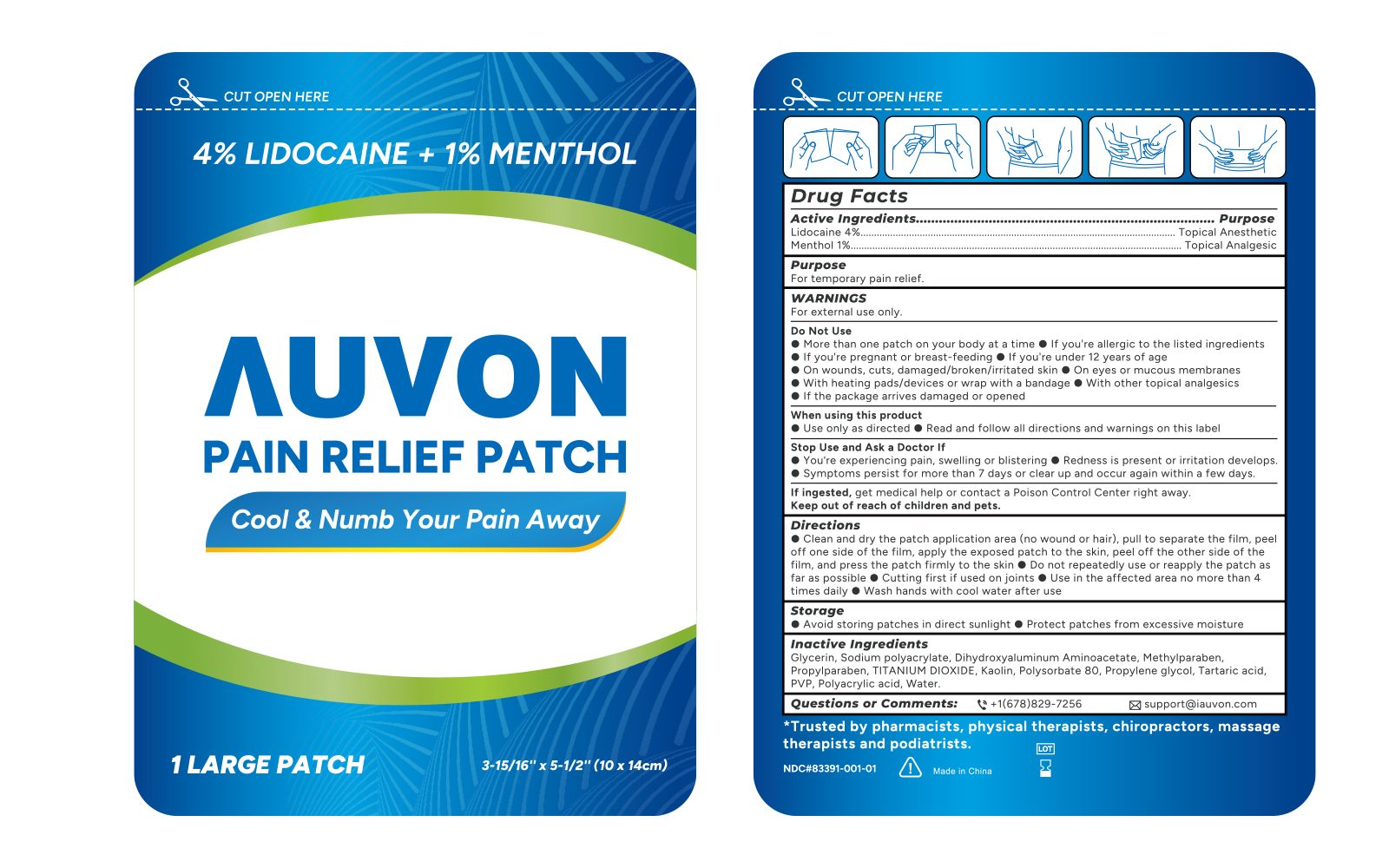 DRUG LABEL: AUVON LIDOCAINE MENTHOL Pain Relief
NDC: 83391-001 | Form: PATCH
Manufacturer: SHENZHEN YUWEN E-COMMERCE CO., LTD.
Category: otc | Type: HUMAN OTC DRUG LABEL
Date: 20241205

ACTIVE INGREDIENTS: LIDOCAINE 370 mg/1 1; MENTHOL 100 mg/1 1
INACTIVE INGREDIENTS: GLYCERIN; METHYLPARABEN; SODIUM POLYACRYLATE (2500000 MW); POLYSORBATE 80; PROPYLENE GLYCOL; DIHYDROXYALUMINUM AMINOACETATE ANHYDROUS; SILICON DIOXIDE; TARTARIC ACID; TITANIUM DIOXIDE; WATER; PROPYLPARABEN; KAOLIN; POLYACRYLIC ACID (250000 MW)

83391-001

AUVON LIDOCAINE MENTHOL Pain Relief Patch

Drug Facts

Active ingredients

Lidocaine 4%

Menthol 1%

Purposes

Topical anesthetic

Topical analgesic

Use

for the temporary pain relief

Warnings

For external use only

Do not use

- If you are allergic to the listed ingredients
- If you are pregnent or breast feeding
- If you are under 12 years of age
- On wounds, cuts, damaged/broken/irritated skin
- On eyes or mucous membranes
- With heating pads/devices or wrap with a bandage
- With other topical analgesics
- If the package arrives damaged or opened.

When using this product

■ Use only as directed

■ Read and follow all directions and warnings on this label

■ avoid contact with the eyes and mucous membranes

■ rare cases of serious burns have been reported with products of this type

■ a transient burning sensation may occur upon application but generally disappears in several days

■ dispose of used patch in manner that always keeps product away from children and pets. Used patches still

contain the drug product that can produce serious adverse effects if a child or pet chews or ingests this patch.

Stop use and ask a doctor if

You are experiencing pain, swelling or blistering

Redness is persent or irritation develops

Symptoms persist for more than 7 days or clear up and occur again within a few days

Keep out of reach of children and pets.

If ingested, get medical help or contact a Poison Control Center

right away.

Directions

■ Clean and dry the patch application area (no wound or hair), pull to separate the film, peel off one side of the film, apply the exposed patch to the skin, peel off the other side of the film, and press the patch firmly to the skin.

■ Do not repeatedly use or repeatedly reapply the patch as far as possible

■ Cut first if if used on joints

■ Use in te affected area no more than 4 times daily

■ Wash hands with cool water after use

Storage

- Avoid storing patches in direct sunlight
- Protect patches from excessive moisture

Inactive ingredients

Glycerin, sodium polyacrylate, dihydroxyaluminum aminoacetate, methylparaben, propylparaben, polyacrylic acid, Kaolin, polysorbate 80, propylene glycol, tartaric acid, PVP, titanium dioxide, water, petrolatum, CMC, mineral oil